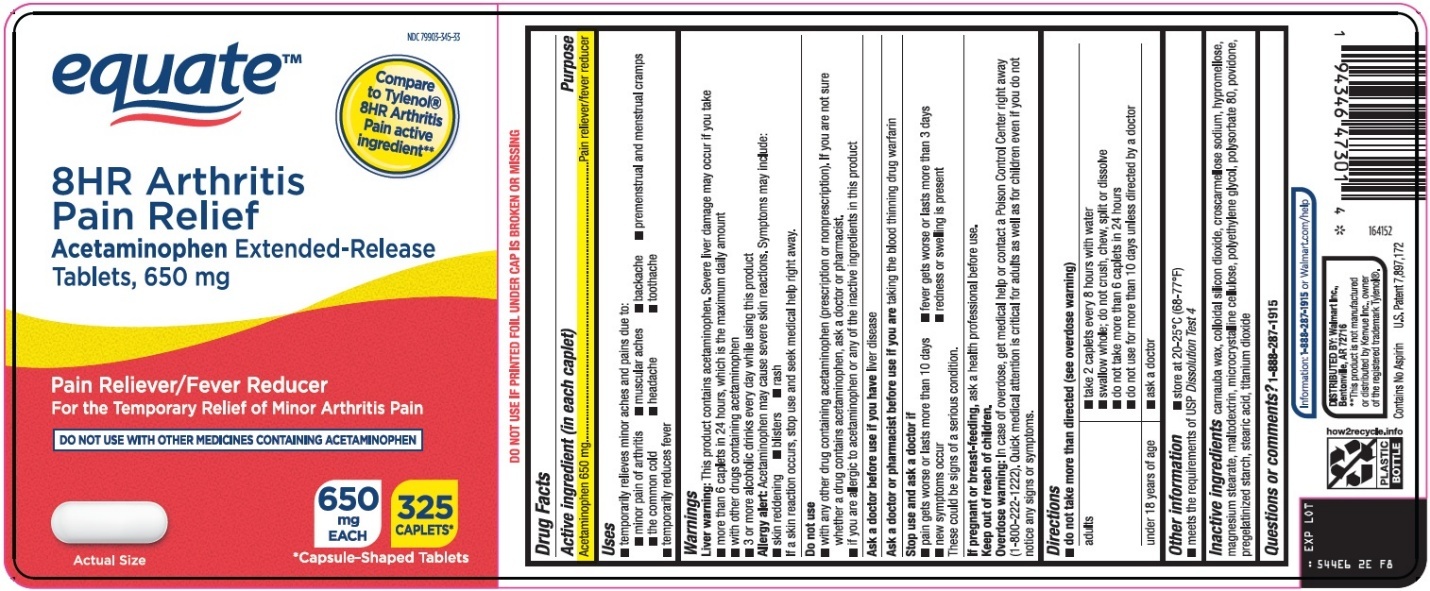 DRUG LABEL: equate 8hr arthritis pain relief
NDC: 79903-345 | Form: TABLET, FILM COATED, EXTENDED RELEASE
Manufacturer: WALMART INC.
Category: otc | Type: HUMAN OTC DRUG LABEL
Date: 20260209

ACTIVE INGREDIENTS: ACETAMINOPHEN 650 mg/1 1
INACTIVE INGREDIENTS: CARNAUBA WAX; SILICON DIOXIDE; CROSCARMELLOSE SODIUM; HYPROMELLOSE, UNSPECIFIED; MAGNESIUM STEARATE; MALTODEXTRIN; MICROCRYSTALLINE CELLULOSE; POLYETHYLENE GLYCOL, UNSPECIFIED; POLYSORBATE 80; POVIDONE, UNSPECIFIED; STEARIC ACID; TITANIUM DIOXIDE

Wal-Mart 8HR Arthritis Pain Relief Drug Facts

Active ingredient (in each caplet)

Acetaminophen 650 mg

Purpose

Pain reliever/fever reducer

Uses

- temporarily relieves minor aches and pains due to:
  - minor pain of arthritis
  - muscular aches
  - backache
  - premenstrual and menstrual cramps
  - the common cold
  - headache
  - toothache
- temporarily reduces fever

Warnings

Liver warning: This product contains acetaminophen. Severe liver damage may occur if you take

- more than 6 caplets in 24 hours, which is the maximum daily amount
- with other drugs containing acetaminophen
- 3 or more alcoholic drinks every day while using this product

Allergy alert: Acetaminophen may cause severe skin reactions. Symptoms may include:

- skin reddening
- blisters
- rash

If a skin reaction occurs, stop use and seek medical help right away.

Do not use

- with any other drug containing acetaminophen (prescription or nonprescription). If you are not sure whether a drug contains acetaminophen, ask a doctor or pharmacist.
- if you are allergic to acetaminophen or any of the inactive ingredients in this product

Ask a doctor before use if you have

liver disease

Ask a doctor or pharmacist before use if you are

taking the blood thinning drug warfarin

Stop use and ask a doctor if

- pain gets worse or lasts more than 10 days
- fever gets worse or lasts more than 3 days
- new symptoms occur
- redness or swelling is present

These could be signs of a serious condition.

If pregnant or breast-feeding,

ask a health professional before use.

Keep out of reach of children.

Overdose warning: In case of overdose, get medical help or contact a Poison Control Center right away (1-800-222-1222). Quick medical attention is critical for adults as well as for children even if you do not notice any signs or symptoms.

Directions

- do not take more than directed (see overdose warning)

adults | - take 2 caplets every 8 hours with water - swallow whole; do not crush, chew, split or dissolve - do not take more than 6 caplets in 24 hours - do not use for more than 10 days unless directed by a doctor
under 18 years of age | - ask a doctor

Other information

- store at 20-25°C (68-77°F)
- meets the requirements of USP Dissolution Test 4

Inactive ingredients

carnauba wax, colloidal silicon dioxide, croscarmellose sodium, hypromellose, magnesium stearate, maltodextrin, microcrystalline cellulose, polyethylene glycol, polysorbate 80, povidone, pregelatinized starch, stearic acid, titanium dioxide

Questions or comments?

1-888-287-1915

Principal Display Panel

equate™

Compare to Tylenol® 8HR Arthritis Pain active ingredient

8HR Arthritis Pain Relief

Acetaminophen Extended-Release Tablets, 650 mg

Pain Reliever/Fever Reducer

For the Temporary Relief of Minor Arthritis Pain

DO NOT USE WITH OTHER MEDICINES CONTAINING ACETAMINOPHEN

Actual Size

650 mg EACH

325 CAPLETS*

*Capsule-Shaped Tablets